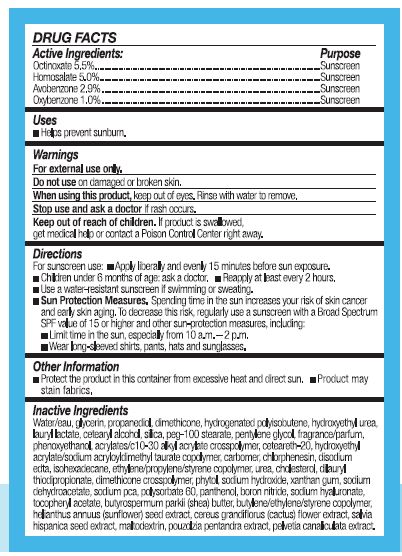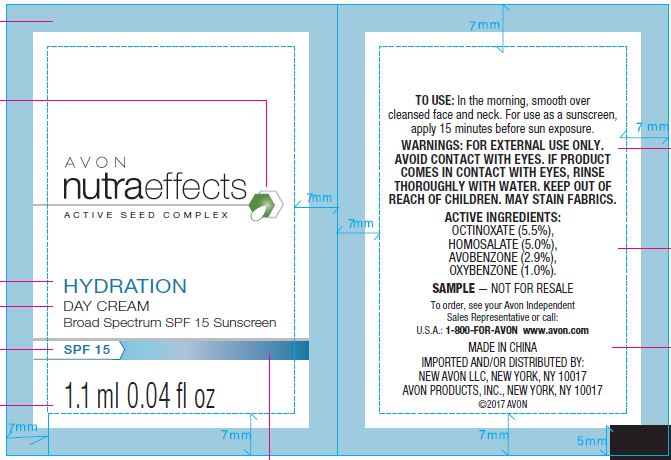 DRUG LABEL: Avon Nutra Effects
NDC: 71110-0012 | Form: CREAM
Manufacturer: Avon Products, Inc.
Category: otc | Type: HUMAN OTC DRUG LABEL
Date: 20180601

ACTIVE INGREDIENTS: OCTINOXATE 55 mg/1 g; HOMOSALATE 50 mg/1 g; AVOBENZONE 29 mg/1 g; OXYBENZONE 10 mg/1 g
INACTIVE INGREDIENTS: DILAURYL THIODIPROPIONATE; SODIUM DEHYDROACETATE; POLYSORBATE 60; BORON NITRIDE; WATER; GLYCERIN; PROPANEDIOL; ISOHEXADECANE; CHOLESTEROL; PANTHENOL; MALTODEXTRIN; PHYTOL; SODIUM HYDROXIDE; XANTHAN GUM; PENTYLENE GLYCOL; DIMETHICONE; HYDROXYETHYL UREA; LAURYL LACTATE; PEG-100 STEARATE; PHENOXYETHANOL; CHLORPHENESIN

Active Ingredients:

Octinoxate 5.5%......

Homosalate 5.0%....

Avonbenzone 2.9%.....

Oxybenzone 1.0%......

Purpose

............Sunscreen

............Sunscreen

............Sunscreen

............Sunscreen

Uses

Helps prevent sunburn.

Warnings

For external use only.

Do not use on damaged or broken skin.

When using this product, keep out of eyes. Rinse with water to remove.

Stop use and ask a doctor if rash occurs.

KEEP OUT OF REACH OF CHILDREN

Keep our of reach of children. If product is swallowed, get medical help or contact a Poison Control Center right away.

Directions

For suncreen use:

Apply liberally and evenly 15 minutes before sun exposure.
Children under 6 months of age: ask a doctor.
Reapply at least every 2 hours.
Use a water-resistant sunscreen if swimming or sweating.
Sun Protection Measures. Spending time in the sun increases your risk of skin cancer and early skin aging. To decrease this risk, regularly use a sunscreen with a Broad Spectrum SPF value of 15 or higher and other sun-procteion measures, including:
Limite time in the sun, expecially from 10 a.m.-2 p.m.
Wear long-sleeved shirts, pants, hats and sunglasses.

Other Information

- Protect the product in this container from excessive heat and direct sun,
- Product may stain fabrics.

Inactive ingredients

WATER/EAU, GLYCERIN, PROPANEDIOL, DIMETHICONE, HYDROGENATED POLYISOBUTENE, HYDROXYETHYL UREA, LAURYL LACTATE, CETEARYL ALCOHOL, SILICA, PEG-100 STEARATE, PENTYLENE GLYCOL, FRAGRANCE/PARFUM, PHENOXYETHANOL, ACRYLATES/C10-30 ALKYL ACRYLATE CROSSPOLYMER, CETEARETH-20, HYDROXYETHYL ACRYLATE/SODIUM ACRYLOYLDIMETHYL TAURATE COPOLYMER, CARBOMER, CHLORPHENESIN, DISODIUM EDTA, ISOHEXADECANE, ETHYLENE/PROPYLENE/STYRENE COPOLYMER, UREA, CHOLESTEROL, DILAURYL THIODIPROPIONATE, DIMETHICONE CROSSPOLYMER, PHYTOL, SODIUM HYDROXIDE, XANTHAN GUM, SODIUM DEHYDROACETATE, SODIUM PCA, POLYSORBATE 60, PANTHENOL, BORON NITRIDE, SODIUM HYALURONATE, TOCOPHERYL ACETATE, BUTYROSPERMUM PARKII (SHEA) BUTTER, BUTYLENE/ETHYLENE/STYRENE COPOLYMER,

HELIANTHUS ANNUUS (SUNFLOWER) SEED EXTRACT, CEREUS GRANDIFLORUS (CACTUS) FLOWER EXTRACT, SALVIA HISPANICA SEED EXTRACT, MALTODEXTRIN, POUZOLZIA PENTANDRA EXTRACT, PELVETIA CANALICULATA EXTRACT.